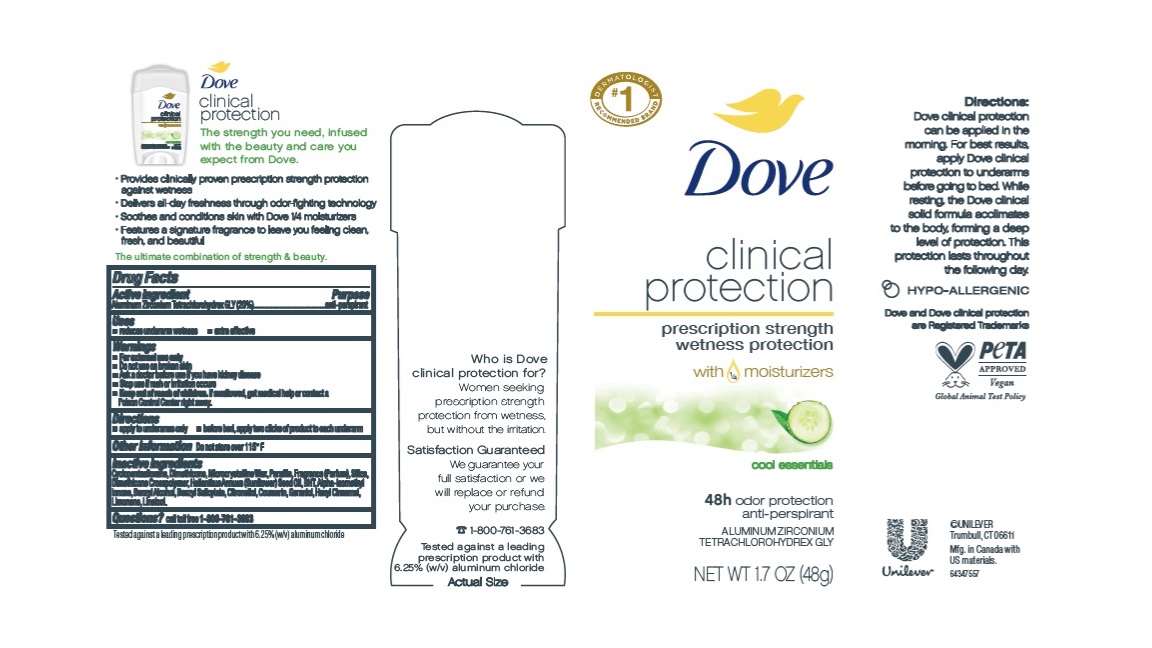 DRUG LABEL: Dove
NDC: 64942-2268 | Form: STICK
Manufacturer: Conopco Inc. d/b/a/ Unilever
Category: otc | Type: HUMAN OTC DRUG LABEL
Date: 20241024

ACTIVE INGREDIENTS: ALUMINUM ZIRCONIUM TETRACHLOROHYDREX GLY 20 g/100 g
INACTIVE INGREDIENTS: BENZYL SALICYLATE; BENZYL ALCOHOL; .ALPHA.-HEXYLCINNAMALDEHYDE; LINALOOL, (+/-)-; ISOMETHYL-.ALPHA.-IONONE; .BETA.-CITRONELLOL, (R)-; COUMARIN; MICROCRYSTALLINE WAX; PARAFFIN; SUNFLOWER OIL; CYCLOMETHICONE 5; BUTYLATED HYDROXYTOLUENE; SILICON DIOXIDE; DIMETHICONE; DIMETHICONE CROSSPOLYMER (450000 MPA.S AT 12% IN CYCLOPENTASILOXANE); LIMONENE, (+)-; GERANIOL

Dove Clinical Protection Cool Essentials Antiperspirant & Deodorant

Drug Facts

Active ingredient

Aluminum Zirconium Tetrachlorohydrex GLY (20.0 %)

Purpose

antiperspirant

Uses

• reduces underarm wetness
• extra effective

Warnings

• For external use only.
• Do not use on broken skin .
• Ask a doctor before use if you have kidney disease.
• Stop use if rash or irritation occurs.

• Keep out of reach of children.

If swallowed, get medical help or contact a Poison Control Center right away.

Directions

• apply to underarms only
• before bed, apply two clicks of product to each underarm

Other information

Do not store over 115°F

Inactive ingredients

Cyclopentasiloxane, Dimethicone, Microcrystalline Wax, Paraffin, Fragrance (Parfum), Silica, Dimethicone Crosspolymer, Helianthus Annuus (Sunflower) Seed Oil, BHT, Alpha-Isomethyl Ionone, Benzyl Alcohol, Benzyl Salicylate, Citronellol, Coumarin, Geraniol, Hexyl Cinnamal, Limonene, Linalool

Questions?

Call toll-free 1-800-761-3683